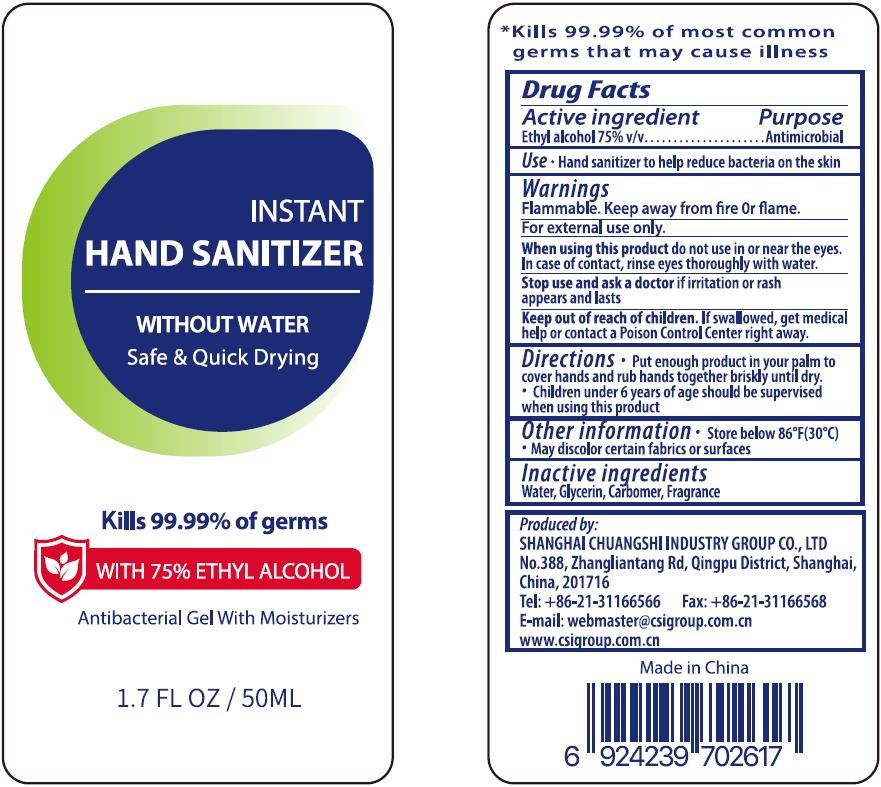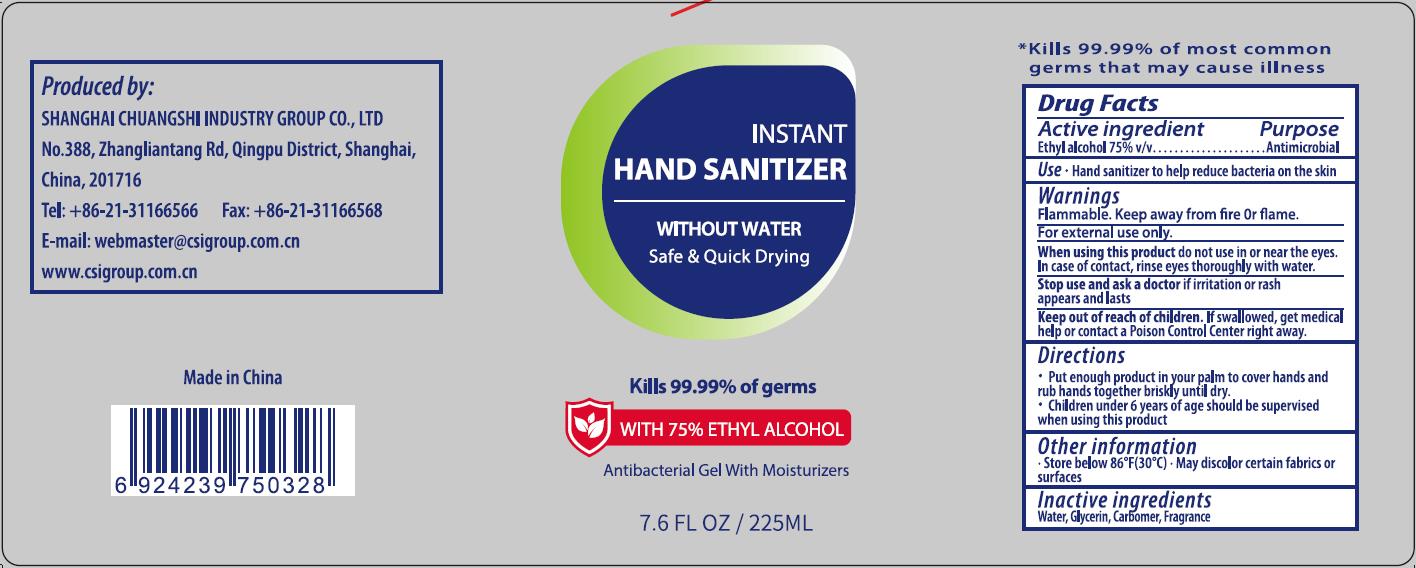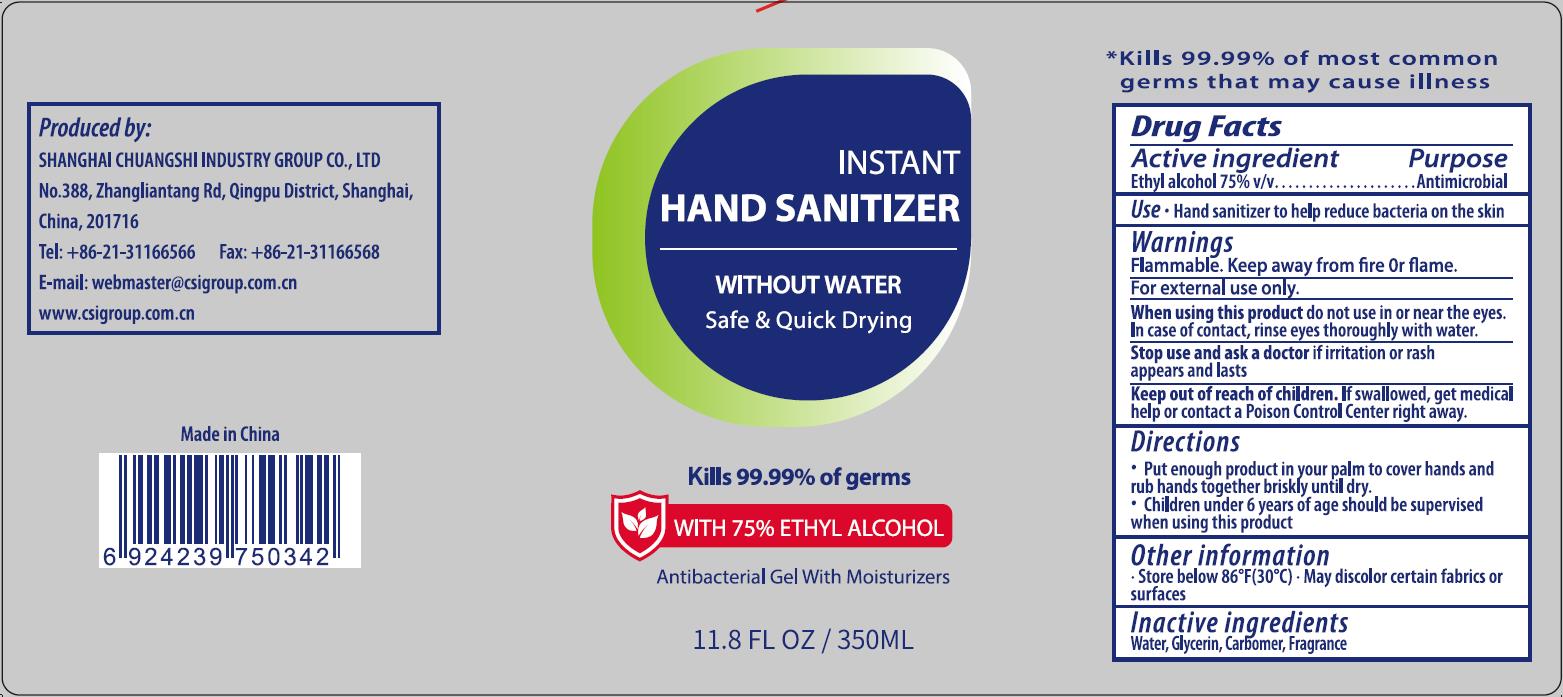 DRUG LABEL: INSTANT HAND SANITIZER
NDC: 73557-237 | Form: GEL
Manufacturer: Shanghai Chuangshi Industry Group Co., Ltd
Category: otc | Type: HUMAN OTC DRUG LABEL
Date: 20200429

ACTIVE INGREDIENTS: ALCOHOL 262.5 mL/350 mL
INACTIVE INGREDIENTS: GLYCERIN; WATER; CARBOMER HOMOPOLYMER, UNSPECIFIED TYPE; CLOVE

INSTANT HAND SANITIZER, Alcohol 75%

Active Ingredient(s)

Ethyl alcohol 75% v/v. Purpose: Antimicrobial

Purpose

Antimicrobial

Use

Hand sanitizer to help reduce bacteria on the skin.

Warnings

Flammable.

Keep away from heat or flame.

For external use only.

Do not use

When using this product, do not use in or near the eyes.

In case of contact, rinse eyes thoroughly with water.

When using this product do not use in or near the eyes.

In case of contact, rinse eyes thoroughly with water.

Stop use and ask a doctor if irritation or rash appears or lasts.

Keep out of reach of children. If swallowed, get medical help or contact a Poison Control Center right away.

Directions

- Put enough product in your palm to cover hands and rub hands together briskly until dry.
- Children under 6 years of age should be supervised when using this product.

Other information

- Store below 86℉ (30℃).
- May discolor certain fabrics or surfaces.

Inactive ingredients

Water, Glycerin, Carbomer, Fragrance.